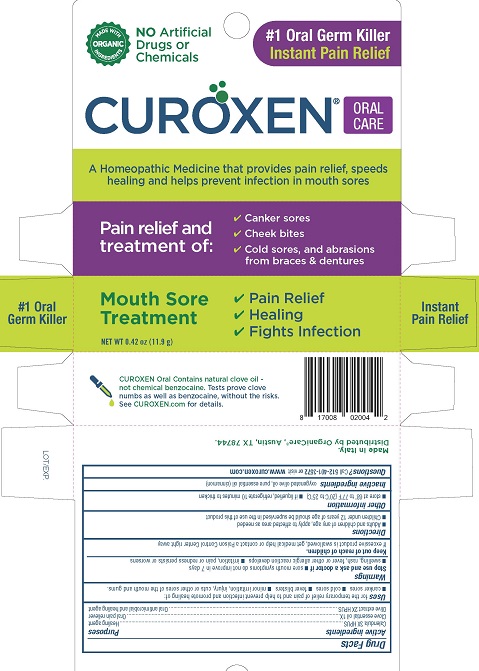 DRUG LABEL: Curoxen Oral Care
NDC: 71042-004 | Form: OINTMENT
Manufacturer: OrganiCare Nature's Science, LLC
Category: homeopathic | Type: HUMAN OTC DRUG LABEL
Date: 20251020

ACTIVE INGREDIENTS: CLOVE OIL 1 [hp_X]/12 g; OLEA EUROPAEA FRUIT VOLATILE OIL 2 [hp_X]/12 g; CALENDULA OFFICINALIS FLOWERING TOP 3 [hp_X]/12 g
INACTIVE INGREDIENTS: CINNAMON OIL; OLIVE OIL

CUROXEN ORAL CARE

Drug Facts

Active ingredients

Calendula 3X HPUS

Clove essential oil 1X

Olive extract 2X HPUS

Purposes

Healing agent

Oral pain reliever

Oral antimicrobial and healing agent

Uses

for the temporary relief of pain and to help prevent infection and promote healing of:

- canker sores
- cold sores
- fever blisters
- minor irritation, injury, cuts or other sores of the mouth and gums.

Warnings

Stop use and ask a doctor if

- sore mouth symptoms do not improve in 7 days
- swelling, rash, fever or other allergic reaction develops
- irritation, pain or redness persists or worsens

Keep out of reach of children. If excessive product is swallowed, get medical help or contact a Poison Control Center right away.

Directions

- Adults and children of any age, apply to the affected area as needed
- Children under 12 years of age should be supervised in the use of this product

Other information

- store at 68° to 77°F (20° to 25°C)
- if liquefied, refrigerate 10 minutes to thicken

Inactive ingredients

oxygenated olive oil, pure essential oil (cinnamon)

Questions?

Call 512-401-3572 or visit www.curoxen.com

Made in Italy

Distributed by OrganiCare®, Austin, TX 78744

PACKAGE LABEL

MADE WITH ORGANIC INGREDIENTS

NO Artificial Drugs or Chemicals

#1 Oral Germ Killer

Instant Pain Relief

CUROXEN® ORAL CARE

A Homeopathic Medicine that provides pain relief, speeds healing, and helps prevent Infection in mouth sores

Pain relief and treatment of:

- Canker sores
- Cheek bites
- Cold sores, and abrasions from braces & dentures

Mouth Sore Treatment

- Pain Relief
- Healing
- Fights Infection

NET WT 0.42 oz (11.9 g)